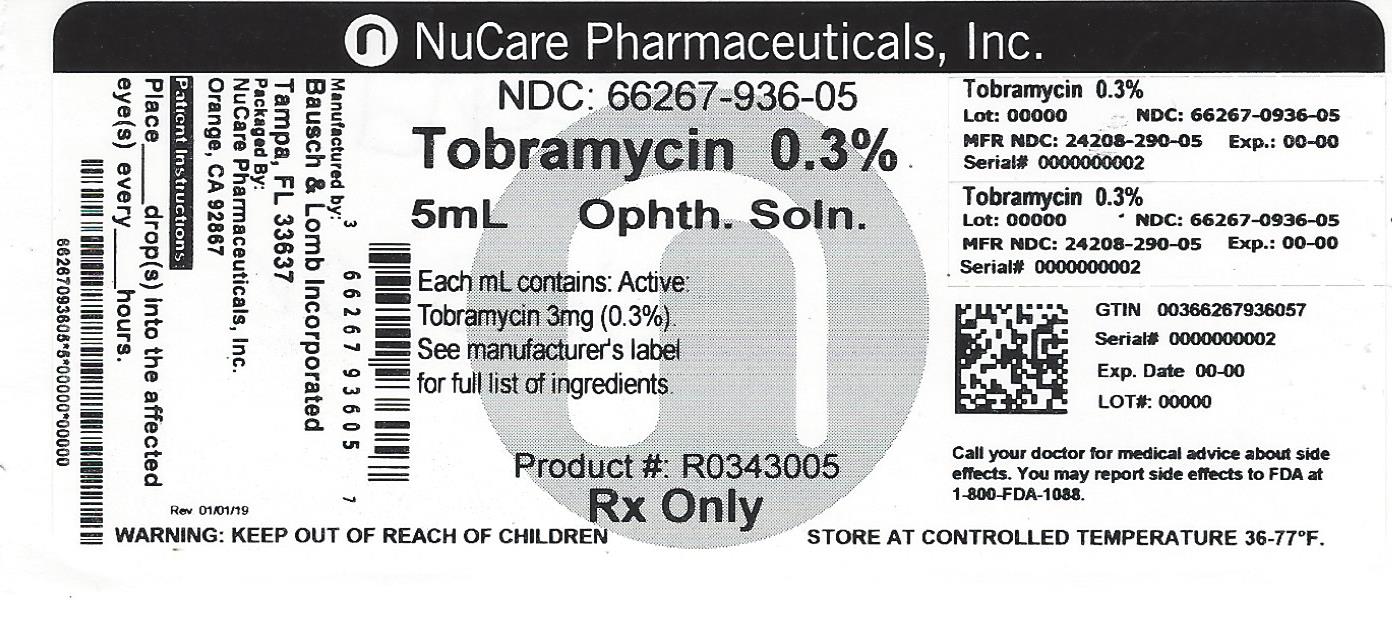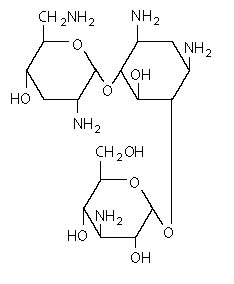 DRUG LABEL: Tobramycin
NDC: 66267-936 | Form: SOLUTION
Manufacturer: NuCare Pharmaceuticals,Inc.
Category: prescription | Type: HUMAN PRESCRIPTION DRUG LABEL
Date: 20240814

ACTIVE INGREDIENTS: TOBRAMYCIN 3 mg/1 mL
INACTIVE INGREDIENTS: BORIC ACID; WATER; SODIUM CHLORIDE; SODIUM HYDROXIDE; SODIUM SULFATE; SULFURIC ACID; TYLOXAPOL

Tobramycin
Ophthalmic Solution, USP
0.3% (Sterile)

Rx only

DESCRIPTION

Tobramycin Ophthalmic Solution, USP 0.3% is a sterile topical ophthalmic antibiotic formulation prepared specifically for topical therapy of external ophthalmic infections.

Each mL contains

Active: Tobramycin 3 mg (0.3%). Inactives: Boric Acid, Sodium Sulfate, Sodium Chloride, Tyloxapol and Purified Water. Sodium Hydroxide and/or Sulfuric Acid (to adjust pH). Tobramycin Ophthalmic Solution, USP 0.3% has a pH range between 7.0 and 8.0.

Preservative Added: Benzalkonium Chloride 0.1 mg (0.01%).

Tobramycin is a water-soluble aminoglycoside antibiotic active against a wide variety of gram-negative and gram-positive ophthalmic pathogens.

The chemical structure of tobramycin is

Molecular weight: 467.52

Molecular formula: C18H37N5O9

Chemical name:

(2S,3R,4S,5S,6R)-4-amino-2-[(1S,2S,3R,4S,6R)-4,6-diamino-3-[(2R,3R,5S,6R)-3-amino-6-(aminomethyl)-5-hydroxyoxan-2-yl]oxy-2-hydroxycyclohexyl]oxy-6-(hydroxymethyl)oxane-3,5-diol;sulfuric acid

CLINICAL PHARMACOLOGY

In Vitro Data: In vitro studies have demonstrated tobramycin is active against susceptible strains of the following microorganisms: Staphylococci, including S. aureus and S. epidermidis (coagulase-positive and coagulase-negative), including penicillin-resistant strains.

Streptococci, including some of the Group A-beta-hemolytic species, some nonhemolytic species, and some Streptococcus pneumoniae.

Pseudomonas aeruginosa, Escherichia coli, Klebsiella pneumoniae, Enterobacter aerogenes, Proteus mirabilis, Morganella morganii, most Proteus vulgaris strains, Haemophilus influenzae and H. aegyptius, Moraxella lacunata, Acinetobacter calcoaceticus and some Neisseria species. Bacterial susceptibility studies demonstrate that in some cases, microorganisms resistant to gentamicin retain susceptibility to tobramycin.

INDICATIONS AND USAGE

Tobramycin Ophthalmic Solution, USP 0.3% is a topical antibiotic indicated in the treatment of external infections of the eye and its adnexa caused by susceptible bacteria. Appropriate monitoring of bacterial response to topical antibiotic therapy should accompany the use of Tobramycin Ophthalmic Solution, USP 0.3%. Clinical studies have shown tobramycin to be safe and effective for use in children.

CONTRAINDICATIONS

Tobramycin Ophthalmic Solution, USP 0.3% is contraindicated in patients with known hypersensitivity to any of its components.

WARNINGS

FOR TOPICAL OPHTHALMIC USE ONLY - NOT FOR INJECTION INTO THE EYE

Sensitivity to topically applied aminoglycosides may occur in some patients. If a sensitivity reaction to Tobramycin Ophthalmic Solution, USP 0.3% occurs, discontinue use.

PRECAUTIONS

General

As with other antibiotic preparations, prolonged use may result in overgrowth of nonsusceptible organisms, including fungi. If superinfection occurs, appropriate therapy should be initiated. Cross-sensitivity to other aminoglycoside antibiotics may occur; if hypersensitivity develops with this product, discontinue use and institute appropriate therapy. Patients should be advised not to wear contact lenses if they have signs and symptoms of bacterial conjunctivitis.

Information For Patients

Do not touch dropper tip to any surface, as this may contaminate the solution.

Pregnancy Category B

Reproduction studies in three types of animals at doses up to thirty-three times the normal human systemic dose have revealed no evidence of impaired fertility or harm to the fetus due to tobramycin. There are, however, no adequate and well-controlled studies in pregnant women. Because animal studies are not always predictive of human response, this drug should be used during pregnancy only if clearly needed.

Nursing Mothers

Because of the potential for adverse reactions in nursing infants from Tobramycin Ophthalmic Solution, USP 0.3%, a decision should be made whether to discontinue nursing the infant or discontinue the drug, taking into account the importance of the drug to the mother.

Pediatric Use

Safety and effectiveness in pediatric patients below the age of two months has not been established.

Geriatric Use

No overall clinical differences in safety or effectiveness have been observed between elderly and younger patients.

ADVERSE REACTIONS

The most frequent adverse reactions to Tobramycin Ophthalmic Solution are hypersensitivity and localized ocular toxicity, including lid itching and swelling, and conjunctival erythema. These reactions occur in less than three of 100 patients treated with tobramycin. Similar reactions may occur with the topical use of other aminoglycoside antibiotics. Other adverse reactions have not been reported from tobramycin therapy; however, if topical ocular tobramycin is administered concomitantly with systemic aminoglycoside antibiotics, care should be taken to monitor the total serum concentration.

To report SUSPECTED ADVERSE REACTIONS, contact Bausch + Lomb, a division of Valeant Pharmaceuticals North America LLC, at 1-800-321-4576 or FDA at 1-800-FDA-1088 or www.fda.gov/medwatch.

OVERDOSAGE

Clinically apparent signs and symptoms of an overdose of Tobramycin Ophthalmic Solution, USP 0.3% (punctate keratitis, erythema, increased lacrimation, edema and lid itching) may be similar to adverse reaction effects seen in some patients.

DOSAGE AND ADMINISTRATION

In mild to moderate disease, instill one or two drops into the affected eye(s) every four hours. In severe infections, instill two drops into the eye(s) hourly until improvement, following which treatment should be reduced prior to discontinuation.

DO NOT USE IF IMPRINTED NECKBAND IS NOT INTACT.

FOR TOPICAL OPHTHALMIC USE ONLY

HOW SUPPLIED

Tobramycin Ophthalmic Solution, USP 0.3% is supplied in a plastic bottle with a controlled drop tip and a white polypropylene cap in the following size:

NDC 66267-936-05 Box of 5mL

Storage

Store at 2°-25°C (36°-77°F). Avoid excessive heat.

KEEP OUT OF REACH OF CHILDREN.

Revised June 2017

Bausch + Lomb, a division of Valeant Pharmaceuticals North America LLC, Bridgewater, NJ 08807 USA

©Bausch & Lomb Incorporated

9116805 (folded)

9116905 (flat)